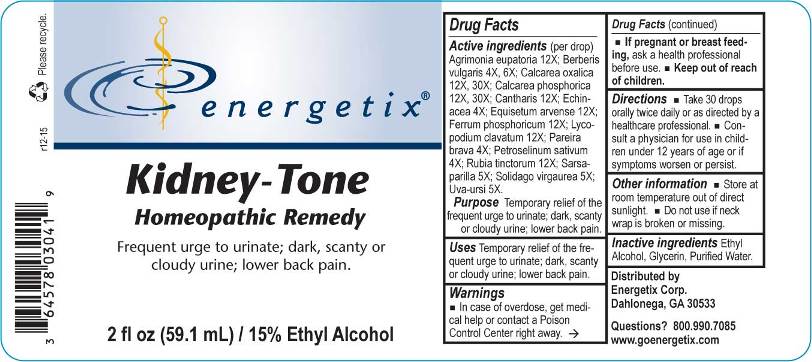 DRUG LABEL: Kidney-Tone
NDC: 64578-0084 | Form: LIQUID
Manufacturer: Energetix Corp
Category: homeopathic | Type: HUMAN OTC DRUG LABEL
Date: 20160107

ACTIVE INGREDIENTS: AGRIMONIA EUPATORIA WHOLE 12 [hp_X]/1 mL; BERBERIS VULGARIS ROOT BARK 4 [hp_X]/1 mL; CALCIUM OXALATE MONOHYDRATE 12 [hp_X]/1 mL; TRIBASIC CALCIUM PHOSPHATE 12 [hp_X]/1 mL; LYTTA VESICATORIA 12 [hp_X]/1 mL; ECHINACEA ANGUSTIFOLIA 4 [hp_X]/1 mL; EQUISETUM ARVENSE TOP 12 [hp_X]/1 mL; FERRUM PHOSPHORICUM 12 [hp_X]/1 mL; LYCOPODIUM CLAVATUM SPORE 12 [hp_X]/1 mL; CHONDRODENDRON TOMENTOSUM ROOT 4 [hp_X]/1 mL; PETROSELINUM CRISPUM 4 [hp_X]/1 mL; RUBIA TINCTORUM ROOT 12 [hp_X]/1 mL; SARSAPARILLA 5 [hp_X]/1 mL; SOLIDAGO VIRGAUREA FLOWERING TOP 5 [hp_X]/1 mL; ARCTOSTAPHYLOS UVA-URSI LEAF 5 [hp_X]/1 mL
INACTIVE INGREDIENTS: WATER; GLYCERIN; ALCOHOL

Drug Facts:

ACTIVE INGREDIENTS:

Agrimonia Eupatoria 12X, Berberis Vulgaris 4X, 6X, Calcarea Oxalica 12X, 30X, Calcarea Phosphorica 12X, 30X, Cantharis 12X, Echinacea 4X, Equisetum Arvense 12X, Ferrum Phosphoricum 12X, Lycopodium Clavatum 12X, Pareira Brava 4X, Petroselinum Sativum 4X, Rubia Tinctorum 12X, Sarsaparilla 5X, Solidago Virgaurea 5X, Uva-Ursi 5X.

PURPOSE:

Temporary relief of frequent urge to urinate; dark, scanty or cloudy urine; lower back pain.

WARNINGS:

In case of overdose, get medical help or call a Poison Control Center right away.
If pregnant or breast-feeding, ask a health professional before use.
Keep out of reach of children.

Other Information
Store in cool, dry place out of direct sunlight.
Do not use if neck wrap is broken or missing.

Keep out of reach of children. In case of overdose, contact physician or Poison Control Center right away.

DIRECTIONS:

Take 30 drops orally twice daily or as directed by a healthcare professional.

Consult a physician for use in children under 12 years of age.

USES:

Temporary relief of frequent urge to urinate; dark, scanty or cloudy urine; lower back pain.

INACTIVE INGREDIENTS:

Purified Water, Glycerin, 15% Ethyl Alcohol.

QUESTIONS:

Distributed by

Energetix Corp

Dahlonega, GA 30533

Questions? 800.990.7085

PACKAGE LABEL DISPLAY:

energetix

Kidney-Tone

Homeopathic Remedy

Frequent urge to urinate; dark, scanty or

cloudy urine; lower back pain.

2 fl oz (59.1 mL)